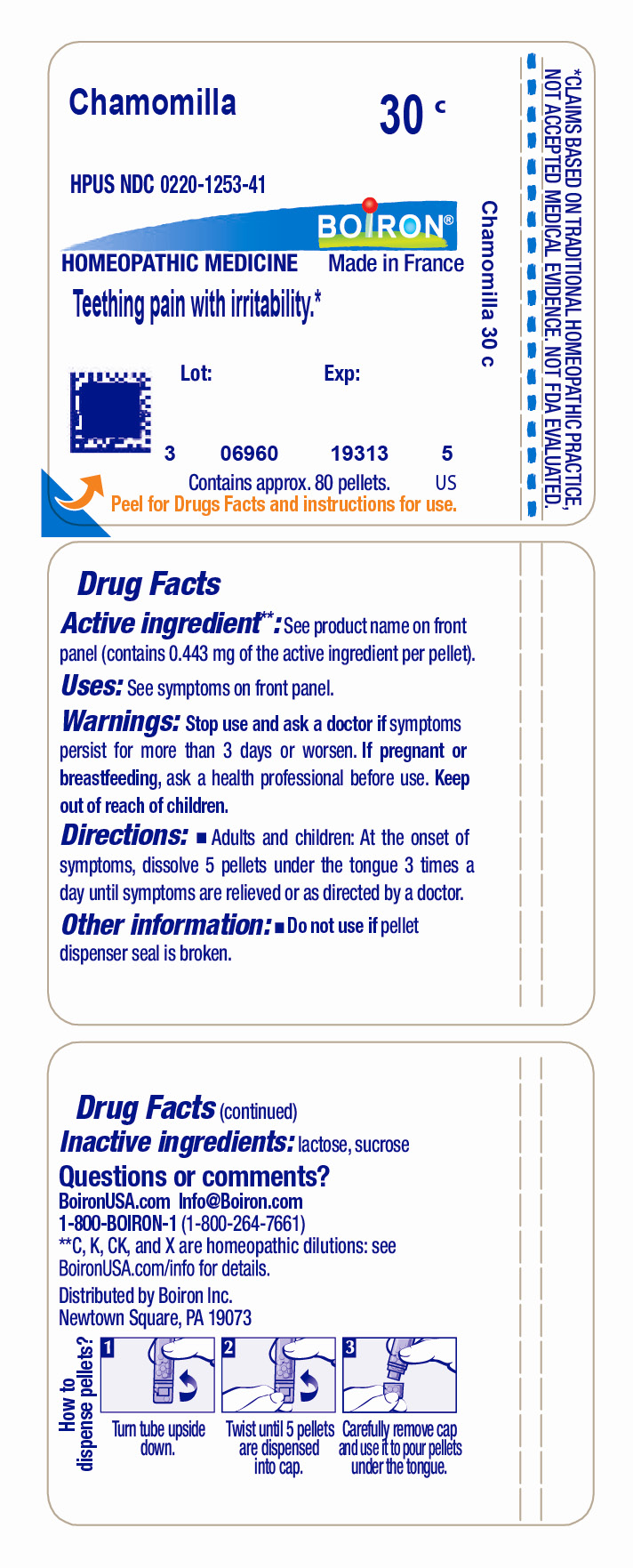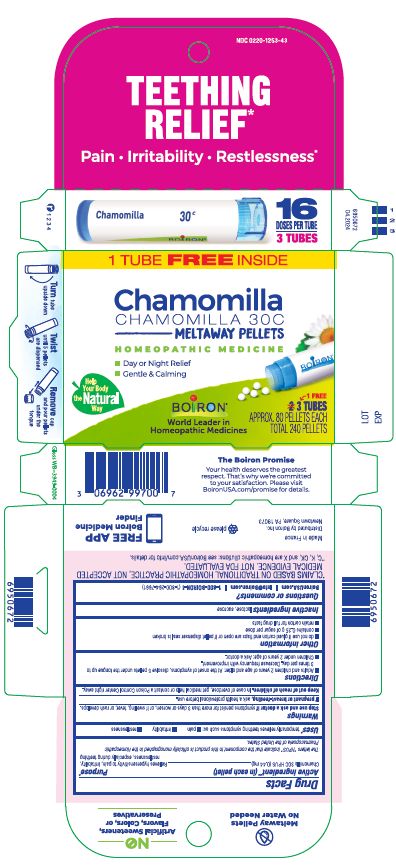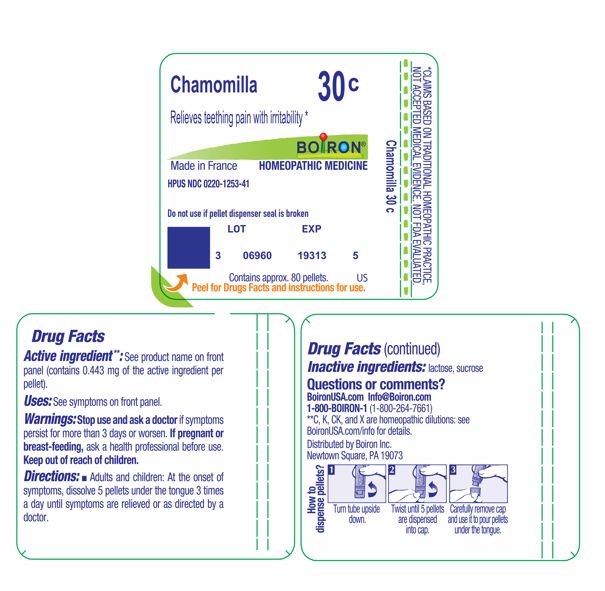 DRUG LABEL: Chamomilla
NDC: 0220-1253 | Form: PELLET
Manufacturer: Boiron
Category: homeopathic | Type: HUMAN OTC DRUG LABEL
Date: 20240722

ACTIVE INGREDIENTS: MATRICARIA CHAMOMILLA 30 [hp_C]/30 [hp_C]
INACTIVE INGREDIENTS: LACTOSE, UNSPECIFIED FORM; SUCROSE

Chamomilla 30C

ACTIVE INGREDIENT

Chamomilla 30C HPUS

(**contains 0.443 mg of the active ingredient per pellet)

The letters "HPUS" indicate that the components in this product are officially monographed in the Homeopathic Pharmacopoeia of the United States.

PURPOSE

Relieves hypersensitivity to pain, irritability, restlessness, especially during teething

INDICATIONS AND USAGE

Teething Relief Uses*

temporarily relieves teething symptoms such as

- pain
- irritability
- restlessness

Tube Uses*

Relieves teething pain with irritability *

STOP USE

Teething Relief Box

Stop use and ask a doctor if symptoms persist for more than 3 days or worsen, or if swelling, fever, or rash develops.

Tube

Stop use and ask a doctor if symptoms persist for more than 3 days or worsen.

PREGNANCY OR BREAST FEEDING

If pregnant or breast-feeding, ask a health professional before use.

Keep out of reach of children. In case of overdose, get medical help or contact a Poison Control Center right away.

Teething Relief Box

Teething Relief*

Pain Irritability Restlessness*

3 Tubes

Approx 80 pellets each

16 Doses per tube

Total 240 pellets

do not use if glued carton end flaps are open or if pellet dispenser seal is broken

contains 0.25 g of sugar per dose

retain carton for full drug facts

Turn tube upside down, Twist until 5 pellets are dispensed. Remove the cap and use it to pour pellets under tongue.

Tube

Do not use if pellet dispenser seal is broken.
Contains approx 80 pellets.
How to dispense pellets? Turn tube upside down. Twist until 5 pellets are dispensed into cap. Carefully remove the cap and use it to pour pellets under the tongue.

*CLAIMS BASED ON TRADITIONAL HOMEOPATHIC PRACTICE NOT ACCEPTED MEDICAL EVIDENCE. NOT FDA EVALUATED.
*C,K,CK, and X are homeopathic dilutions: see BoironUSA.com/info for details.

INACTIVE INGREDIENT

lactose, sucrose

DOSAGE AND ADMINISTRATION

Teething Relief Box

Adults and children 2 years of age and older: At the onset of symptoms, dissolve 5 pellets under the tongue up to 3 times per day. Decrease frequency with improvement.

Children under 2 years of age: Ask a doctor.

Tube

Adults and children: At the onset of symptoms, dissolve 5 pellets under the tongue 3 times a day until symptoms are relieved or as directed by a doctor.

QUESTIONS

BoironUSA.com Info@boiron.com
1-800-BOIRON-1 (1-800-264-7661)
Distributed by Boiron, Inc.
Newtown Square, PA 19073